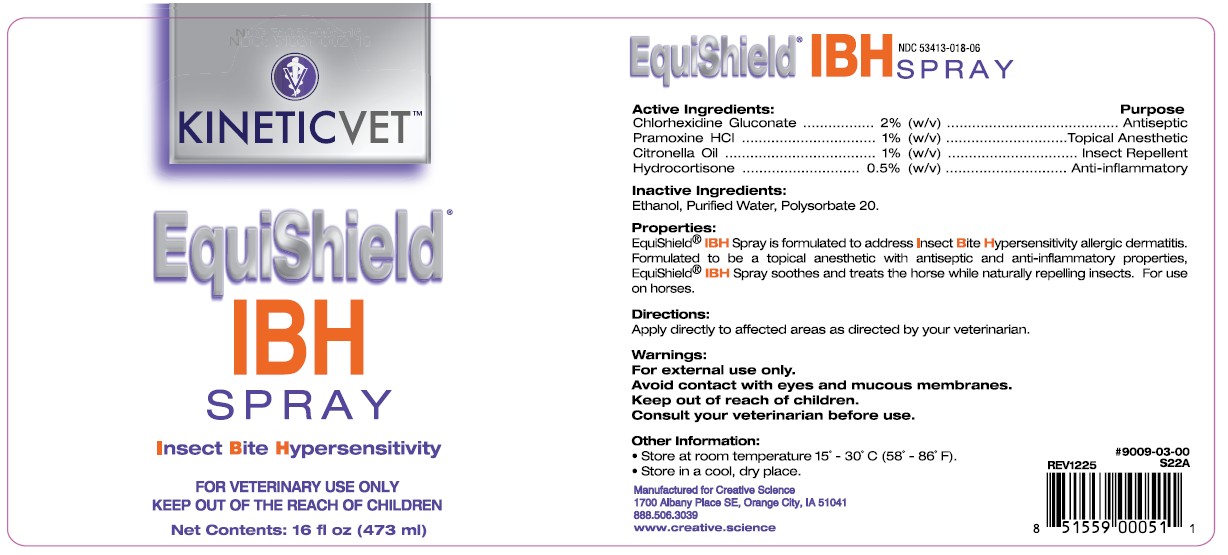 DRUG LABEL: EquiShield IBH
NDC: 53413-018 | Form: SPRAY
Manufacturer: Creative Science
Category: animal | Type: OTC ANIMAL DRUG LABEL
Date: 20251217

ACTIVE INGREDIENTS: CHLORHEXIDINE GLUCONATE 2 g/100 mL; PRAMOXINE HYDROCHLORIDE 1 g/100 mL; CITRONELLA OIL 1 g/100 mL; HYDROCORTISONE 0.5 g/100 mL

EquiShield IBH Spray

NDC 53413-018-06

Active Ingredients:

Chlorhexidine Gluconate ........... 2% (w/v)

Pramoxine HCL ........................ 1% (w/v)

Citronella Oil ........................... 1% (w/v)

Hydrocortisone ..................... 0.5% (w/v)

Purpose

Antiseptic

Topical Anesthetic

Insect Repellent

Anti-Inflammatory

Inactive Ingredients:

Ethanol, Purified Water, Polysorbate 20

Properties:

EquiShield® IBH Spray is formulated to address Insect Bite Hypersensitivity allergic dermatitis. Formulated to be a topical anesthetic with antiseptic and anti-inflammatory properties, EquiShield® IBH Spray soothes and treats the horse while naturally repelling insects. For use on horses.

Directions:

Apply directly to affected areas as directed by your veterinarian.

Warnings:

For external use only.

Avoid contact with eyes and mucous membranes.

Consult your veterinarian before use.

Keep out of reach of children.

Other Information:

• Store at room temperature 15˚ - 30˚C (58˚ - 86˚F).
• Store in a cool, dry place.

#9009-03-00

REV1225 S22A

UPC 851559000511

Manufactured for Creative Science

1700 Albany Place SE, Orange City, IA 51041

888.506.3039

www.creative.science

PACKAGE LABEL

EquiShield® IBH SPRAY

Insect Bite Hypersensitivity

FOR VETERINARY USE ONLY

KEEP OUT OF THE REACH OF CHILDREN

Net Contents: 16 fl oz (473 ml)